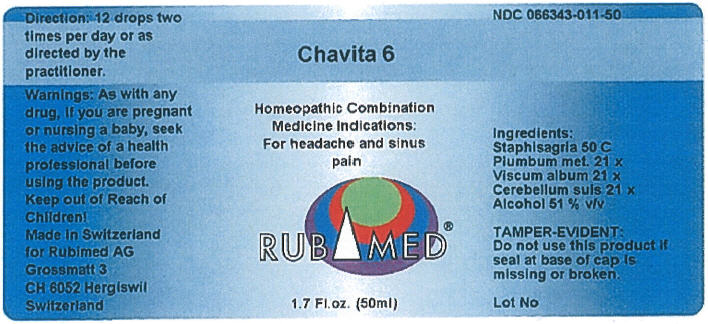 DRUG LABEL: Chavita 6
NDC: 66343-011 | Form: LIQUID
Manufacturer: RUBIMED AG
Category: otc | Type: HUMAN OTC DRUG LABEL
Date: 20150707

ACTIVE INGREDIENTS: DELPHINIUM STAPHISAGRIA SEED 50 [hp_C]/1 mL; LEAD 21 [hp_X]/1 mL; VISCUM ALBUM FRUITING TOP 21 [hp_X]/1 mL; SUS SCROFA CEREBELLUM 21 [hp_X]/1 mL
INACTIVE INGREDIENTS: ALCOHOL 0.51 mL/1 mL

Chavita 6

PURPOSE

INDICATIONS AND USAGE

Homeopathic Combination Medicine Indications: For headache and sinus pain

Ingredients

INACTIVE INGREDIENT

Staphisagria 50 C
Plumbum met. 21 x
Viscum album 21 x
Cerebellum suis 21 x
Alcohol 51 % v/v

TAMPER-EVIDENT

Do not use this product if seal at base of cap is missing or broken.

Direction

12 drops two times per day or as directed by the practitioner.

Warnings

PREGNANCY OR BREAST FEEDING

As with any drug, if you are pregnant or nursing a baby, seek the advice of a health professional before using the product.

Keep out of Reach of Children!

PRINCIPAL DISPLAY PANEL - 50 ml Bottle Label

Chavita 6

Homeopathic Combination
Medicine Indications:
For headache and sinus
pain

RUBIMED®

1.7 Fl.oz. (50ml)